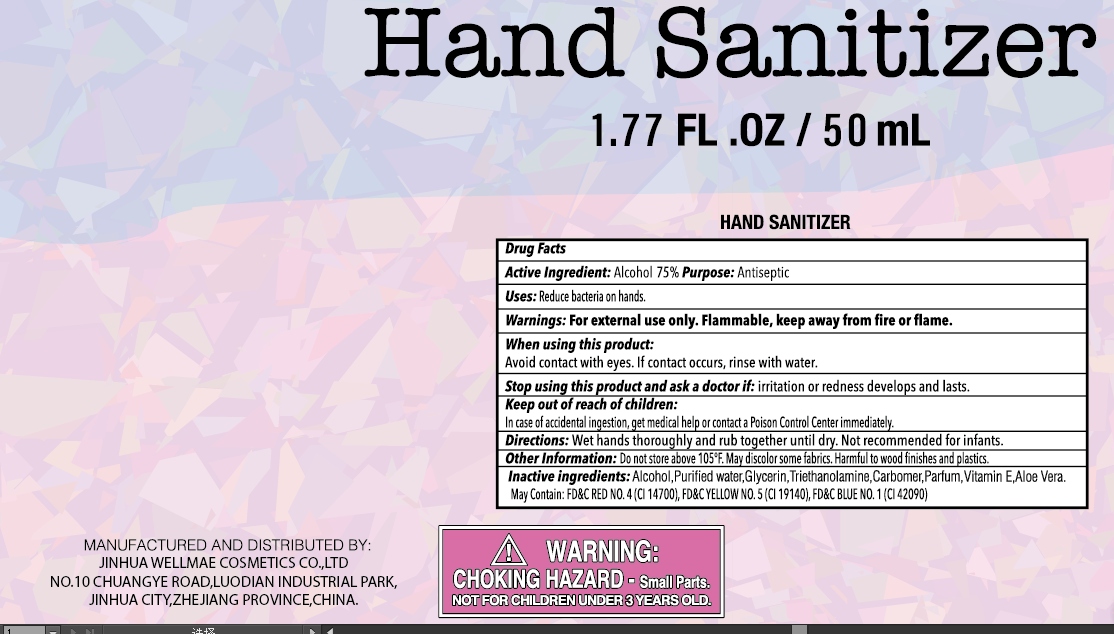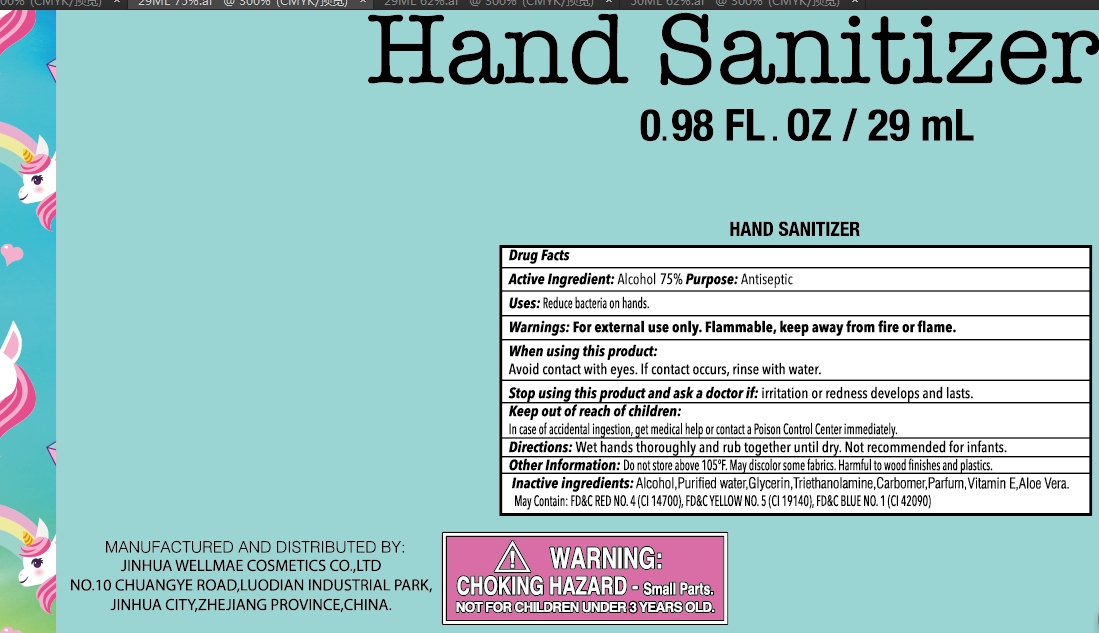 DRUG LABEL: Hand Sanitizer
NDC: 75427-002 | Form: GEL
Manufacturer: Jinhua City Wellmae Cosmetics Co., Ltd.
Category: otc | Type: HUMAN OTC DRUG LABEL
Date: 20220119

ACTIVE INGREDIENTS: ALCOHOL 75 mL/100 mL
INACTIVE INGREDIENTS: PROPYLENE GLYCOL; CARBOMER COPOLYMER TYPE A; WATER

75427-002
Hand Sanitizer

Active Ingredient(s)

Active Ingredient: Alcohol 62% Purpose: Antiseptic

Purpose

Antiseptic, Hand Sanitizer

Warnings

For external use only. Flammable. Keep away from heat or flame

Do not use

Stop using this product and ask a doctor if: irritation or redness develops and lasts.

When using this product:Avoid contact with eyes. If contact occurs, rinse with water.

STOP USE

Stop using this product and ask a doctor if: irritation or redness develops and lasts.

KEEP OUT OF REACH OF CHILDREN

In case of accidental ingestion, cet med al help or contact a Poison Control Center immediatelly

Directions

- Wet hands thoroughly and rub together until dry. Not recommended for infants

Inactive ingredients

AQUA,Propylene Glycol,Carbopol 940